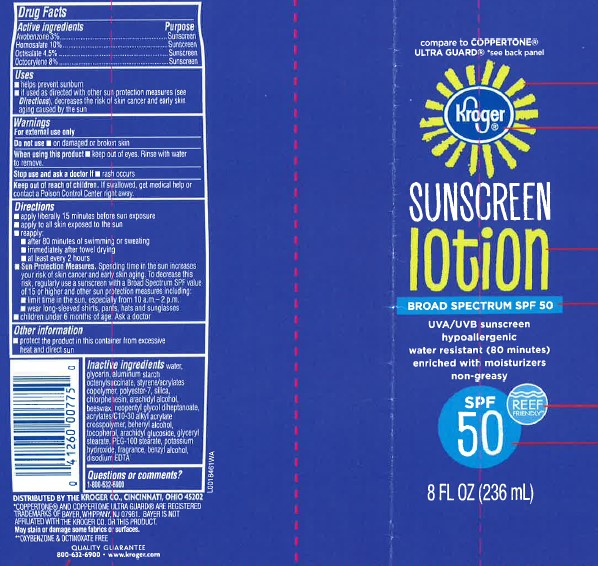 DRUG LABEL: SUNSCREEN
NDC: 30142-940 | Form: LOTION
Manufacturer: The Kroger Co.
Category: otc | Type: HUMAN OTC DRUG LABEL
Date: 20260227

ACTIVE INGREDIENTS: AVOBENZONE 30 mg/1 mL; HOMOSALATE 100 mg/1 mL; OCTISALATE 45 mg/1 mL; OCTOCRYLENE 80 mg/1 mL
INACTIVE INGREDIENTS: WATER; GLYCERIN; ALUMINUM STARCH OCTENYLSUCCINATE; STYRENE/ACRYLAMIDE COPOLYMER (500000 MW); POLYESTER-7; SILICON DIOXIDE; CHLORPHENESIN; ARACHIDYL ALCOHOL; YELLOW WAX; NEOPENTYL GLYCOL DIHEPTANOATE; CARBOMER INTERPOLYMER TYPE A (ALLYL SUCROSE CROSSLINKED); DOCOSANOL; TOCOPHEROL; ARACHIDYL GLUCOSIDE; GLYCERYL MONOSTEARATE; PEG-100 STEARATE; POTASSIUM HYDROXIDE; BENZYL ALCOHOL; EDETATE DISODIUM ANHYDROUS

Kroger 940.000/940AA
Ultra Sunscreen Lotion SPF 50

Active Ingredients

Avobenzone 3%

Homosalate 10%

Octisalate 4.5%

Octocrylene 8%

Purpose

Sunscreen

Use

- helps prevent sunburn
- if used as directed with other sun protections measures (see Directions), decreases the risk of skin cancer and early skin aging caused by the sun

Warnings

For external use only

Do not use

- on damaged or broken skin

When using this product

- keep out of eyes. Rinse with water to remove.

Stop use and ask a doctor if

- rash occurs

Keep out of reach of children.

If swallowed, get medical help or contact a Poison Control Center right away.

Directions

- apply liberally 15 minutes before sun exposure
- apply to all skin exposed to the sun
- reapply:
- after 80 minutes of swimming or sweating
- immediately after towel drying
- at least every 2 hours
- Sun Protection Measures. Spending time in the sun increases your risk of skin cancer and early skin aging. To decrease this risk, regularly use a sunscreen with a Broad Spectrum SPF value of 15 or higher and other sun protection measures including:
- limit time in the sun, especially from 10 a.m. - 2 p.m.
- wear long-sleeved shirts, pants, hats and sunglasses
- children under 6 months of age: Ask a doctor

Other information

- Protect the product in this container from excessive heat and direct sun

Inactive ingredients

water, glycerin, aluminum starch octenylsuccinate, styrene/acrylates copolymer, polyester-7, silica, chlorphenesin, arachidyl alcohol, beeswax, neopentyl glycol diheptanoate, acrylates/C10-30 alkyl acrylate crosspolymer, behenyl alcohol, tocopherol, arachidyl glucoside, glyceryl stearate, PEG-100 stearate, potassium hydroxide, fragrance, benzyl alcohol, disodium EDTA

ADVERSE REACTION

Distributed by the Kroger Co. Cincinnati, Ohio 45202

*Coppertone®and Coppertone Ultra Guard®are registered trademarks of Bayer, Whippany, NJ 07981, Bayer is not affliated with the Kroger Co. or this product.

May stain or damage some fabrics or surfaces.

**oxybenzone & octinoxate free

Quality guarantee

800-632-6900 www.kroger.com

Principal Display Panel

Compare to Coppertone®Ultra Guard®*see back panel

Kroger®

sunscreen lotion

BROAD SPECTRUM SPF 50

UVA/UVB sunscreen

hypoallergenic

water reisistant (80 minutes)

enriched with moisturizers

non-greasy

SPF 50

Reef friendly*

8 FL OZ (236 mL)